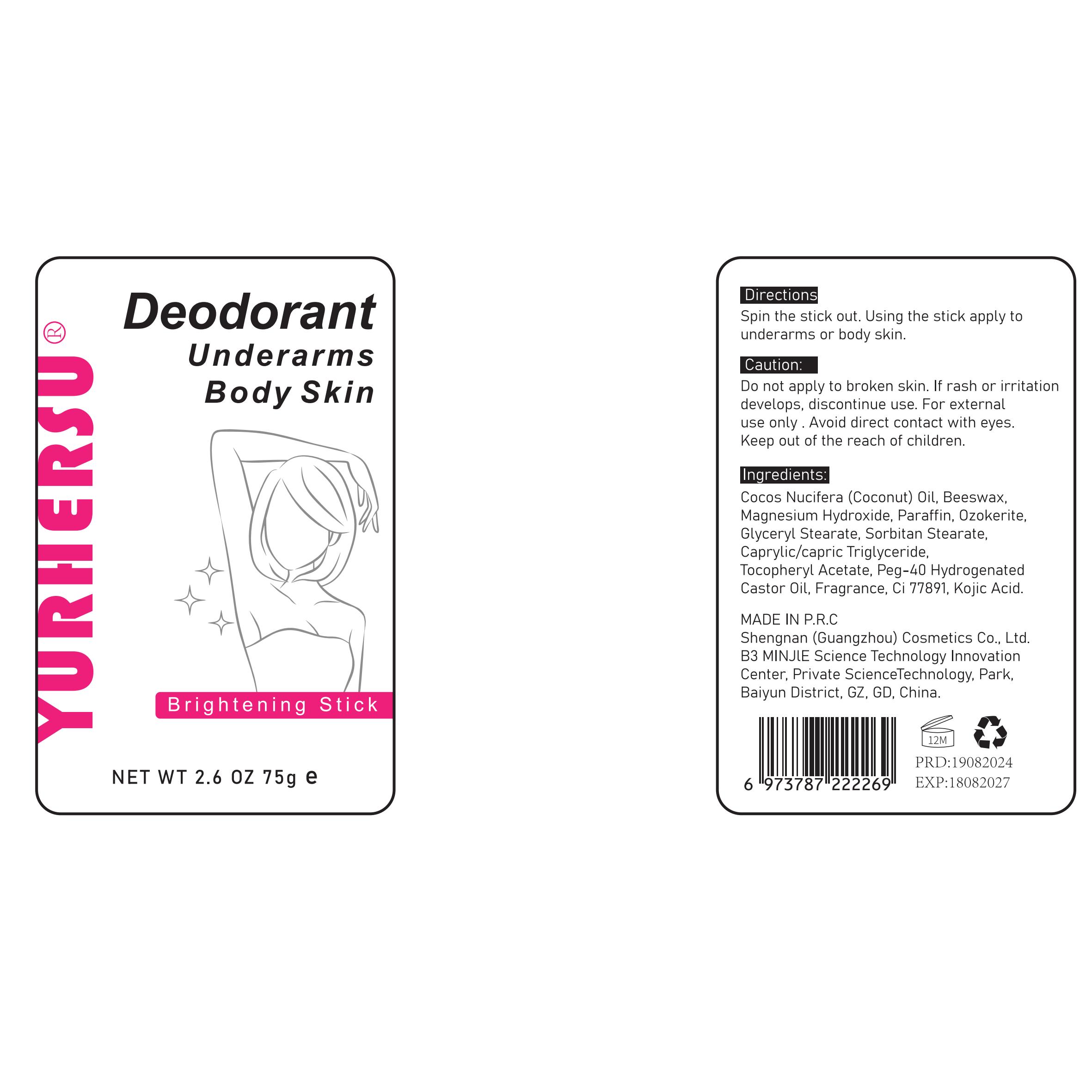 DRUG LABEL: Deodorant Underarms Body Skin
NDC: 84019-008 | Form: PASTE
Manufacturer: Shengnan (Guangzhou) Cosmetics Co., Ltd
Category: otc | Type: HUMAN OTC DRUG LABEL
Date: 20240902

ACTIVE INGREDIENTS: KOJIC ACID 1 g/100 g
INACTIVE INGREDIENTS: HYDROGENATED CASTOR OIL; PEG-8 BEESWAX; CAPRYLIC/CAPRIC/SUCCINIC TRIGLYCERIDE; PARAFFIN; PEG-6 SORBITAN STEARATE; MAGNESIUM HYDROXIDE; FRAGRANCE 13576; PEG-10 GLYCERYL STEARATE

Deodorant Underarms Body Skin

Kojic Acid

Kojic Acid 0.7%

underarm whitening

USAGE

Spin the stick out. Using the stick apply tounderarms or body skin.

Caution

Do not apply to broken skin. lf rash or irritationdevelops,discontinue use.For externaluse only . Avoid direct contact with eyes.Keep out of the reach of children.

Stop use and ask a doctor if

rash occurs

When using thls product

keep out of eyes. Rinse with water to remove.

STOP USE

If swelling,blistering or other discomfort occurs.please stop using and consult doctor immediately
If symptoms have not been relieved after using for more than 7 days.please stop using and consult doctor immediately.

KEEP OUT OF REACH OF CHILDREN

If swallowed,get medical help or contact a Poison Contro1 Center right away.

DOSAGE AND ADMINISTRATION

Twice a day, do not rinse within 2 hours after use.

STORAGE AND HANDLING

protect the product in this container from excessive heat and direct sun

INACTIVE INGREDIENT

Cocos Nucifera (Coconut) Oil 26.5%
Beeswax 15%
Magnesium 15%
Paraffin 10%
Ozokerite 10%
Glyceryl Stearate 7%
Sorbitan Stearate 7%
Caprylic/Capric Triglyceride 5%
Tocopheryl Acetate 1%
PEG-40 Hydrogenated Castor Oil 1%
Fragrance 1%
CI 77891 0.8%
Kojic Acid 0.7%